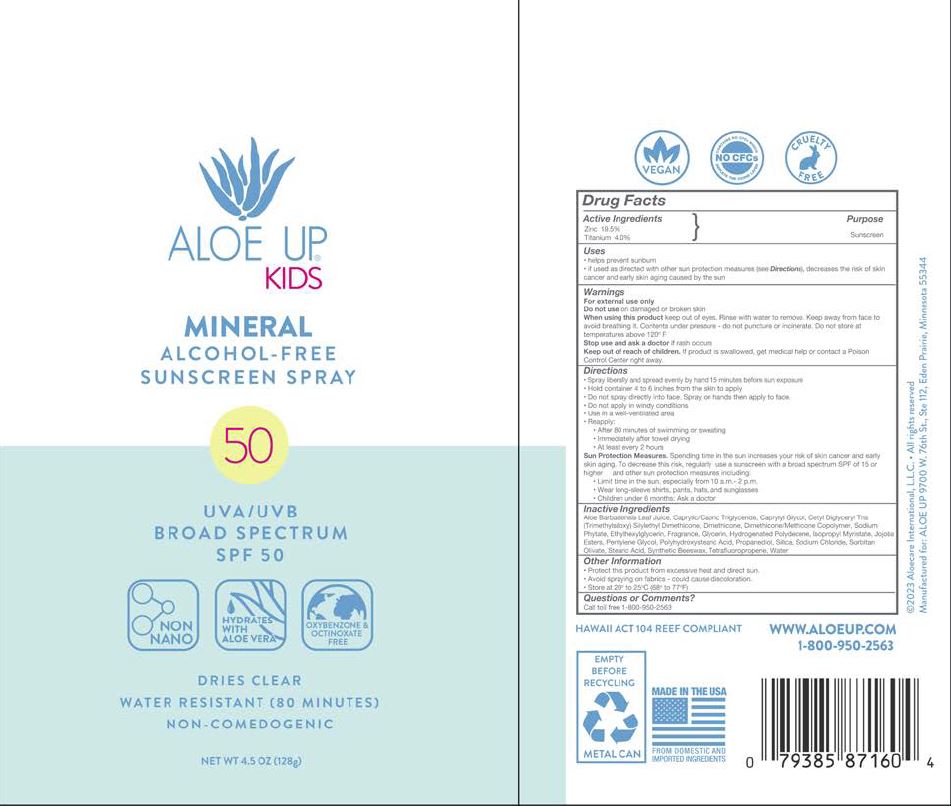 DRUG LABEL: Aloe Up SPF 50 Kids Mineral
NDC: 61477-235 | Form: SPRAY
Manufacturer: Aloe Care International, LLC
Category: otc | Type: HUMAN OTC DRUG LABEL
Date: 20250618

ACTIVE INGREDIENTS: ZINC OXIDE 19.5 g/100 g; TITANIUM DIOXIDE 4 g/100 g
INACTIVE INGREDIENTS: PROPANEDIOL; SILICON DIOXIDE; SODIUM CHLORIDE; SODIUM PHYTATE; SORBITAN OLIVATE; STEARIC ACID; SYNTHETIC BEESWAX; WATER; 2,3,3,3-TETRAFLUOROPROPENE; POLYHYDROXYSTEARIC ACID (2300 MW); ALOE BARBADENSIS LEAF JUICE; CETYL DIGLYCERYL TRIS(TRIMETHYLSILOXY)SILYLETHYL DIMETHICONE (950 MM2/S); DIMETHICONE; HYDROGENATED POLYDECENE (1500 CST); HYDROGENATED JOJOBA OIL, RANDOMIZED; PENTYLENE GLYCOL; CAPRYLYL GLYCOL; CAPRYLIC/CAPRIC TRIGLYCERIDE; ETHYLHEXYLGLYCERIN; ISOPROPYL MYRISTATE; GLYCERIN; FRAGRANCE 13576

Aloe Up SPF 50 Kids Mineral Spray 4.5 oz

ACTIVE INGREDIENT

Zinc: 19.5%

Titanium: 4.0%

PURPOSE

Sunscreen

INDICATIONS AND USAGE

- helps prevent sunburn
- is used as directed with other sun protection measures (See Directions), decreases the risk of skin cancer and early skin aging caused by the sun

WARNINGS

For external use only

Do not use on damaged or broken skin.

When using this product keep out of eyes. Rinse with water to remove. Keep away from face to avoid breathing it. Contents under pressure - do not puncture or incinerate. Do not store at temperatures about 120°F.

Stop use and ask a doctor if rash occurs.

Keep out of reach of children. If product is swallowed, get miedical help or contact a Poison Control Center right away.

DOSAGE AND ADMINISTRATION

- Spray liberally and spread evenly by hand 15 minutes before sun exposure.
- Hold container 4 to 6 inches from skin to apply
- Do not spray directly into face. Spray on hands then apply to face
- Do not apply in windy conditions
- Use in a well-ventilated area
- Reapply:
- After 80 minutes of swimming or sweating
- Immediately after towel drying
- At least every 2 hours
- Sun Protection Measures. Spending time in the sun increases your risk of skin cancer and early skin aging. To decrease this risk, regularly use a sunscreen with broad spectrum SPF of 15 or higher and other sun protection measures including:
- Limit time in the sun, especially from 10 am - 2 pm
- Wear long-sleeve shirts, pants, hats, and sunglasses
- Children under 6 months: Ask a doctor

OTHER SAFETY INFORMATION

- Protect the product from excessive heat and direct sun.
- Avoid spraying on fabrics - could cause discoloration
- Store at 20° to 25°C (68° to 77°F)

INACTIVE INGREDIENT

Aloe Barbadensis Leaf Juice

Caprylic/Capric Triglyceride

Caprylyl Glycol

Cetyl Diglyceryl Tris(Trimethylsiloxy)silylethyl Demethicone

Fragrance

Dimethicone

Ethylhexylglycerin

Glycerin

Hydronated Polydecence

Isopropyl Myristate

Jojoba Esters

Pentylene Glycol

Polyhydroxystearic Acid

Propanediol

Silica

Sodium Chloride

Sodium Phytate

Sorbitan Olivate

Stearic Acid

Synthetic Beeswax

Water

Tetrafluoropropene

Questions or Comments?

Call toll free 1-800-950-2563